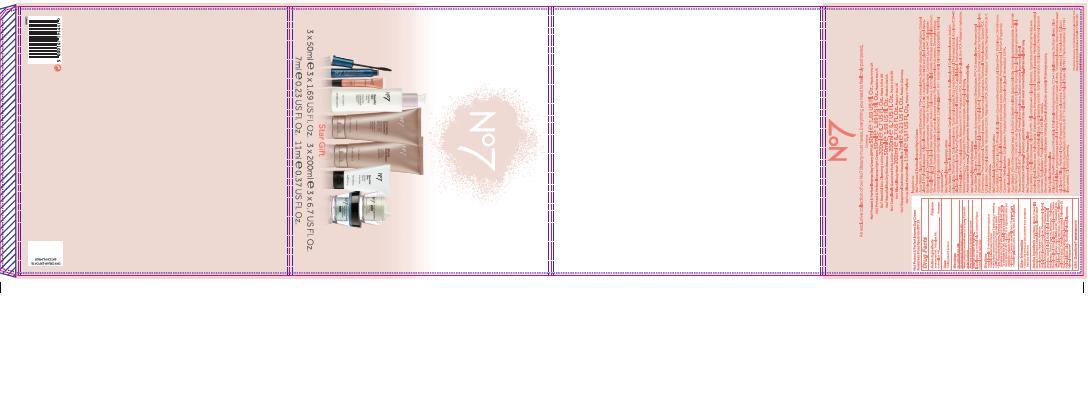 DRUG LABEL: No7 Protect and Perfect Intense Day Cream SPF 15
NDC: 11489-088 | Form: CREAM
Manufacturer: BCM Ltd
Category: otc | Type: HUMAN OTC DRUG LABEL
Date: 20140728

ACTIVE INGREDIENTS: AVOBENZONE 1.5 g/50 g; OCTOCRYLENE 2 g/50 g; OCTISALATE 1 g/50 g
INACTIVE INGREDIENTS: WATER; GLYCERIN; C12-15 ALKYL BENZOATE; DIMETHICONE; CETEARYL GLUCOSIDE; ALUMINUM STARCH OCTENYLSUCCINATE; TRIBEHENIN; AMMONIUM ACRYLOYLDIMETHYLTAURATE/VP COPOLYMER; PHENOXYETHANOL; ALCOHOL; SHEA BUTTER; POTASSIUM CETYL PHOSPHATE; BUTYLENE GLYCOL; METHYLPARABEN; ETHYLPARABEN; XANTHAN GUM; DIPROPYLENE GLYCOL; VITAMIN A PALMITATE; ASCORBYL GLUCOSIDE; HYALURONATE SODIUM; ALFALFA; EDETATE SODIUM; TERT-BUTYL ALCOHOL; LUPINUS ALBUS SEED; PHYLLANTHUS EMBLICA FRUIT; POLYSORBATE 20; POTASSIUM HYDROXIDE; GINKGO BILOBA LEAF OIL; ETHYLHEXYLGLYCERIN; TOCOPHEROL; PALMITOYL OLIGOPEPTIDE; PALMITOYL TETRAPEPTIDE-7

No7 Protect and Perfect INtense Day Cream SPF 15

Carton Active Ingredients Section

Active ingredients

Avobenzone 3%

Octisalate 2%

Octocrylene 4%

Uses

Uses - helps prevent sunburn

Warnings

For external use only

Do not use on damaged or broken skin

When using this product keep out of eyes. Rinse with water to remove.

Ask a doctor

Stop use and ask a doctor if rash occurs

Keep out of reach of children

If swallowed, get medical help or contact a Poison Control Center right away

Directions

Apply liberally 15 minutes before sun exposure

reapply at least every 2 hours

use a water resistnat sunscreen if swimming or sweating

children under 6 months of age: Ask a doctor

Sun Protection Measures. Spending time in the sun increases your risk of skin cancer and early skin aging.

To decrease this risk, regularly use a sunscreen with a Broad Spectrum SPF value of 15 or higher and other sun protection measures including:

Limit time in the sun, especially from 10 a.m - 2 p.m.

wear long-sleeved shirts,pants,hats and sunglasses.

Storage

Other information

Protect the product in this container from excessive heat and direct sun

Inactive ingredients

Aqua(Water), Glycerin, C12-15 alkyl benzoate, Dimethicone, Cetearyl glucoside, Aluminum starch octenylsuccinate, Tribehenin, Ammonium acryloydimethyltaurate/VP copolymer, phenoxyethanol, Alcohol denat., Butyrospermum parkii (Shea) butter, Potassium cetyl phosphate, Cetearyl alcohol, Butylene glycol, Dimethiconol, Methylparaben, Parfum(Fragrance), Xanthan gum, Ethylparaben, Dipropylene glycol, Retinyl palmitate, Ascorbyl glucoside, Sodium hyaluronate, Medicago sativa (Alfalfa) extract, Tetrasodium EDTA, T-butyl alcohol, Lupinus albus seed extract, Carbomer, Phyllanthus emblica fruit extract, Dimethylmethoxy chromanol, Polysorbate 20, Potassium hydroxide, Ginkgo biloba leaf extract, Ethylhexylglycerin, Silica, Tocopherol, Palmitoyl oligopepetide, Palmitoyl tetrapeptide-7.

PATIENT COUNSELING INFORMATION

Made in the UK

The Boots Company PLC Nottingham England NG2 3AA

Dist. by Boots Retail USA Inc. Norwalk CT 06851 USA

www.boots.com